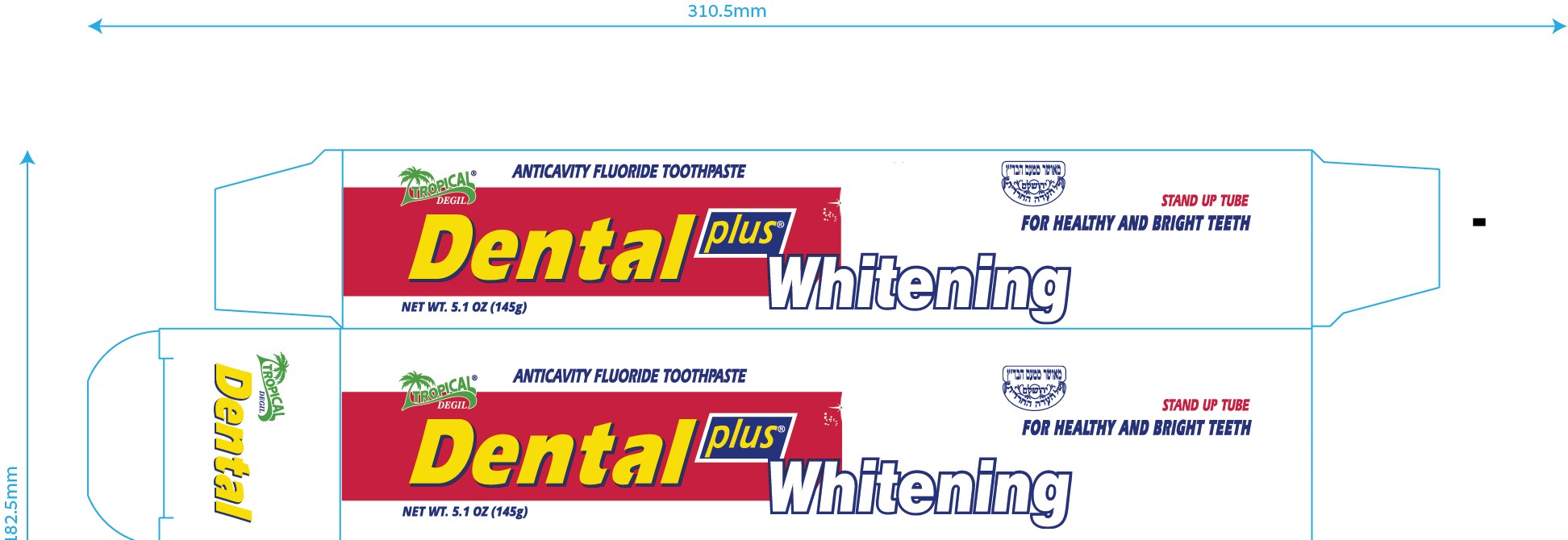 DRUG LABEL: Dental Plus Whitening
NDC: 62685-216 | Form: PASTE
Manufacturer: tropical degil cosmetics industries ltd
Category: otc | Type: HUMAN OTC DRUG LABEL
Date: 20210224

ACTIVE INGREDIENTS: SODIUM MONOFLUOROPHOSPHATE 1 mg/1 g
INACTIVE INGREDIENTS: CALCIUM CARBONATE; POLYETHYLENE GLYCOL 1600; SODIUM LAURYL SULFATE; BENZOIC ACID; ZINC CITRATE; SODIUM BENZOATE; CARBOXYMETHYLCELLULOSE SODIUM; SODIUM BICARBONATE; TITANIUM DIOXIDE; SACCHARIN SODIUM; SORBITOL; WATER; SILICON DIOXIDE

Dental Plus Whitening

Active Ingredient

Sodium monofluorophosphate 0.8% (1,000 ppm F)

Purpose

anticavity

Use

Aids in the prevention of dental cavities

Ask a dentist before use if you have

bleeding or redness lasting more than 2 weeks, pain, swelling, pus, loose teeth, or more spacing between teeth. These may be signs of periodontitis, a serious form of gum disease.

Keep out of reach of children under 6 years of age. If more than used for brushing is accidentally swallowed, get medical help or contact a Poison Control Center right away.

Directions

- Adults and children 2 years of age and older: Brush teeth thoroughly, preferrably after each meal or at least twice a day, or as directed by a dentist or doctor. Instruct children under 6 years of age in good brushing and rinsing habits (to minimize swallowing). Supervise children as necessary until capable of using without supervision.
- Children under 2 years of age: Consult a dentist or doctor.

Inactive ingredients

water, sorbitol, calcium carbonate, silica, PEG-32, sodium lauryl sulphate, flavor, cellulose gum, sodium bicarbonate, flavor, titanium dioxide, sodium saccharin, sodium benzoate, benzoic acid, zinc citrate

Questions or comments? www.sleeksensation.com

PACKAGE LABEL

Dental Plus Whitening

Anticavity Fluoride Toothpaste

Net Wt 5.1 oz (145 g)